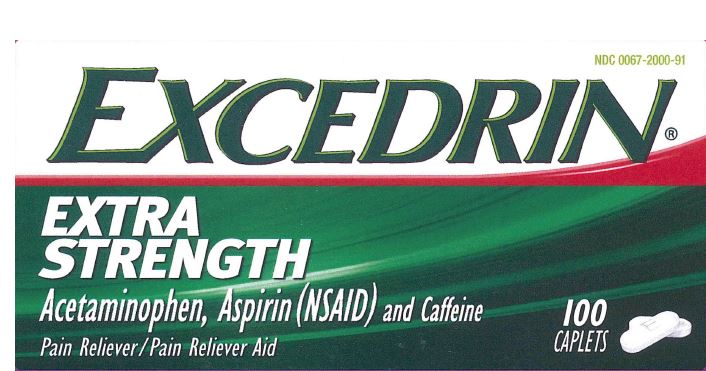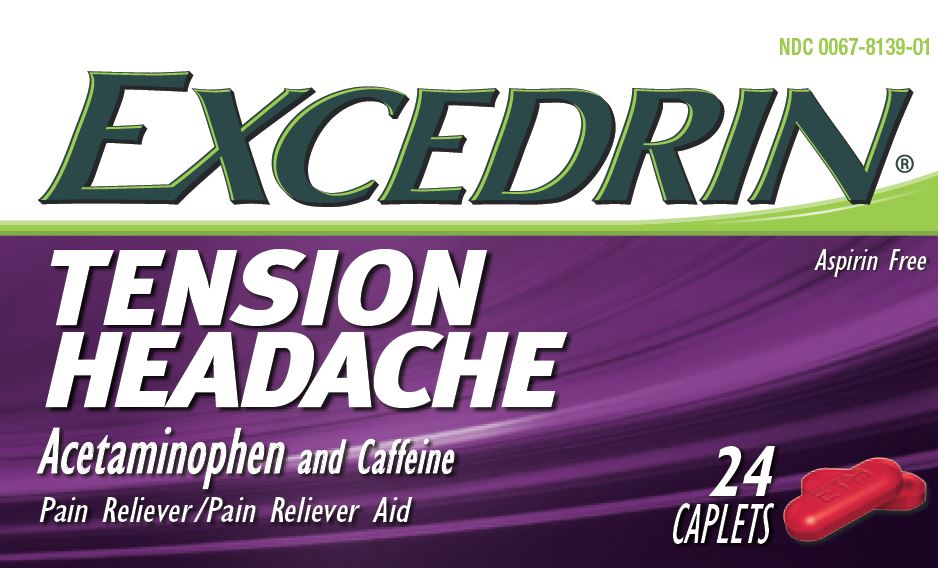 DRUG LABEL: Excedrin Extra Strength and Excedrin Tension Headache
NDC: 0067-8151 | Form: KIT | Route: ORAL
Manufacturer: Haleon US Holdings LLC
Category: otc | Type: HUMAN OTC DRUG LABEL
Date: 20260223

ACTIVE INGREDIENTS: ACETAMINOPHEN 500 mg/1 1; CAFFEINE 65 mg/1 1; ACETAMINOPHEN 250 mg/1 1; ASPIRIN 250 mg/1 1; CAFFEINE 65 mg/1 1
INACTIVE INGREDIENTS: BENZOIC ACID; D&C RED NO. 27 ALUMINUM LAKE; FD&C BLUE NO. 2; FD&C YELLOW NO. 6; MAGNESIUM STEARATE; MICROCRYSTALLINE CELLULOSE; POLYETHYLENE GLYCOL, UNSPECIFIED; POLYVINYL ALCOHOL, UNSPECIFIED; POVIDONE, UNSPECIFIED; STARCH, CORN; STEARIC ACID; TALC; TITANIUM DIOXIDE; BENZOIC ACID; CARNAUBA WAX; FD&C BLUE NO. 1; HYDROXYPROPYL CELLULOSE, UNSPECIFIED; HYPROMELLOSE, UNSPECIFIED; LIGHT MINERAL OIL; MICROCRYSTALLINE CELLULOSE; POLYSORBATE 20; POVIDONE, UNSPECIFIED; PROPYLENE GLYCOL; DIMETHICONE, UNSPECIFIED; SORBITAN MONOLAURATE; STEARIC ACID; TITANIUM DIOXIDE

Drug Facts

Active ingredients (in each caplet)

Acetaminophen 500 mg

Caffeine 65 mg

Purposes

Pain reliever

Pain reliever aid

Uses

- temporarily relieves minor aches and pains due to:
- headache
- muscular aches

Warnings

Allergy alert:Acetaminophen may cause severe skin reactions. Symptoms may include:

- skin reddening
- blisters
- rash

If a skin reaction occurs, stop use and seek medical help right away.

Liver warning:This product contains acetaminophen. Severe liver damage may occur if you take

- more than 6 caplets in 24 hours, which is the maximum daily amount
- with other drugs containing acetaminophen
- 3 or more alcoholic drinks every day while using this product

Caffeine warning:The recommended dose of this product contains about as much caffeine as a cup of coffee. Limit the use of caffeine-containing medications, foods, or beverages while taking this product because too much caffeine may cause nervousness, irritability, sleeplessness, and occasionally, rapid heartbeat.

Do not use

- if you are allergic to acetaminophen
- with any other drug containing acetaminophen (prescription or nonprescription). If you are not sure whether a drug contains acetaminophen, ask a doctor or pharmacist.

Ask a doctor before use if

- you have liver disease

Ask a doctor or pharmacist before use if you are

- taking the blood thinning drug warfarin

Stop use and ask a doctor if

- any new symptoms occur
- painful area is red or swollen
- pain gets worse or lasts for more than 10 days
- fever gets worse or lasts for more than 3 days

These could be signs of a serious condition

If pregnant or breast-feeding,

ask a health professional before use.

Keep out of reach of children.

In case of overdose, get medical help or contact a Poison Control Center right away. Quick medical attention is critical for adults as well as for children even if you do not notice any signs or symptoms.

Directions

- do not use more than directed
- adults and children 12 years and over: take 2 caplets every 6 hours; not more than 6 caplets in 24 hours
- children under 12 years: ask a doctor

Other information

- store at 20°-25°C (68°-77°F).
- close cap tightly after use.
- read all product information before using. Keep this box for important information.

Inactive ingredients

benzoic acid, D&C red no. 27 aluminum lake, FD&C blue no. 2 aluminum lake, FD&C yellow no. 6 aluminum lake, magnesium stearate, microcrystalline cellulose, polyethylene glycol, polyvinyl alcohol, povidone, pregelatinized starch, stearic acid, talc, titanium dioxide

Questions or comments?

1-800-468-7746

Active ingredients (in each caplet)

Acetaminophen 250 mg

Aspirin 250 mg (NSAID*)

Caffeine 65 mg

*nonsteroidal anti-inflammatory drug

Purposes

Pain reliever

Pain reliever

Pain reliever aid

Uses

- temporarily relieves minor aches and pains due to:
  - headache
  - a cold
  - arthritis
  - muscular aches
  - toothache
  - premenstrual & menstrual cramps

Warnings

Reye’s syndrome:Children and teenagers who have or are recovering from chicken pox or flu-like symptoms should not use this product. When using this product, if changes in behavior with nausea and vomiting occur, consult a doctor because these symptoms could be an early sign of Reye’s syndrome, a rare but serious illness.

Allergy alert:Acetaminophen may cause severe skin reactions. Symptoms may include:

- skin reddening
- blisters
- rash

If a skin reaction occurs, stop use and seek medical help right away.

Allergy alert:Aspirin may cause a severe allergic reaction which may include:

- hives
- facial swelling
- asthma (wheezing)
- shock

Liver warning:This product contains acetaminophen. Severe liver damage may occur if you take

- more than 8 caplets in 24 hours, which is the maximum daily amount
- with other drugs containing acetaminophen
- 3 or more alcoholic drinks every day while using this product

Stomach bleeding warning:This product contains an NSAID, which may cause severe stomach bleeding. The chance is higher if you

- are age 60 or older
- have had stomach ulcers or bleeding problems
- take a blood thinning (anticoagulant) or steroid drug
- take other drugs containing prescription or nonprescription NSAIDs (aspirin, ibuprofen, naproxen, or others)
- have 3 or more alcoholic drinks every day while using this product
- take more or for a longer time than directed

Caffeine warning:The recommended dose of this product contains about as much caffeine as a cup of coffee. Limit the use of caffeine-containing medications, foods, or beverages while taking this product because too much caffeine may cause nervousness, irritability, sleeplessness, and occasionally, rapid heart beat.

Do not use

- if you have ever had an allergic reaction to acetaminophen, aspirin or any other pain reliever/fever reducer
- with any other drug containing acetaminophen (prescription or nonprescription). If you are not sure whether a drug contains acetaminophen, ask a doctor or pharmacist.

Ask a doctor before use if

- you have liver disease
- stomach bleeding warning applies to you
- you have a history of stomach problems, such as heartburn
- you have high blood pressure, heart disease, liver cirrhosis, or kidney disease
- you are taking a diuretic
- you have asthma

Ask a doctor or pharmacist before use if you are taking

- a prescription drug for diabetes, gout, or arthritis
- any other drug, or are under a doctor’s care for any serious condition

Stop use and ask a doctor if

- an allergic reaction occurs. Seek medical help right away.
- you experience any of the following signs of stomach bleeding:
  - feel faint
  - vomit blood
  - have bloody or black stools
  - have stomach pain that does not get better
- ringing in the ears or a loss of hearing occurs
- painful area is red or swollen
- pain gets worse or last for more than 10 days
- fever gets worse or lasts for more than 3 days
- any new symptoms occur

These could be signs of a serious condition

If pregnant or breast-feeding,

ask a health professional before use. It is especially important not to use aspirin during the last three months of pregnancy unless definitely directed to do so by a doctor because it may cause problems in the unborn child or complications during delivery.

Keep out of reach of children.

In case of overdose, get medical help or contact a Poison Control Center right away. Quick medical attention is critical for adults as well as for children even if you do not notice any signs or symptoms.

Directions

- do not use more than directed
- drink a full glass of water with each dose
- adults and children 12 years and over: take 2 caplets every 6 hours; not more than 8 caplets in 24 hours
- children under 12 years: ask a doctor

Other information

- store at 20°-25°C (68°-77°F)
- close cap tightly after use
- read all product information before using. Keep this box for important information.

Inactive ingredients

benzoic acid, carnauba wax, FD&C blue #1, hydroxypropylcellulose, hypromellose, light mineral oil, microcrystalline cellulose, polysorbate 20, povidone, propylene glycol, simethicone emulsion, sorbitan monolaurate, stearic acid, titanium dioxide

Questions or comments?

1-800-468-7746

Principal Display Panel (Excedrin Tension Headache)

NDC 0067-8139-01

EXCEDRIN®

TENSION HEADACHE

Acetaminophen and Caffeine

Pain Reliever / Pain Reliever Aid

Aspirin Free

24CAPLETS

TAMPER-EVIDENT BOTTLE

DO NOT USE IF INNER FOIL SEAL IMPRINTED WITH “SEALED for YOUR PROTECTION” IS BROKEN OR MISSING

Distributed by: GSK Consumer Healthcare,

Warren, NJ 07059

©2016 GSK group of companies or its licensor. All rights reserved. Trademarks are owned by or licensed to the GSK group of companies

Visit us at www.excedrin.com

46177299

Principal Display Panel (Excedrin Extra Strength)

NDC 0067-2000-91

EXCEDRIN®

EXTRA STRENGTH

Acetaminophen, Aspirin (NSAID) and Caffeine

Pain Reliever / Pain Reliever Aid

100 CAPLETS

TAMPER-EVIDENT BOTTLE

DO NOT USE IF INNER FOIL SEAL IMPRINTED WITH “SEALED for YOUR PROTECTION” IS BROKEN OR MISSING

Distributed by: GSK Consumer Healthcare,Warren, NJ 07059

©2015 GSK group of companies or its licensor. All rights reserved.

Visit us at www.excedrin.com

DO NOT TAKE BOTH PRODUCTS AT THE SAME TIME. USE PRODUCTS AS DIRECTED.

46172044